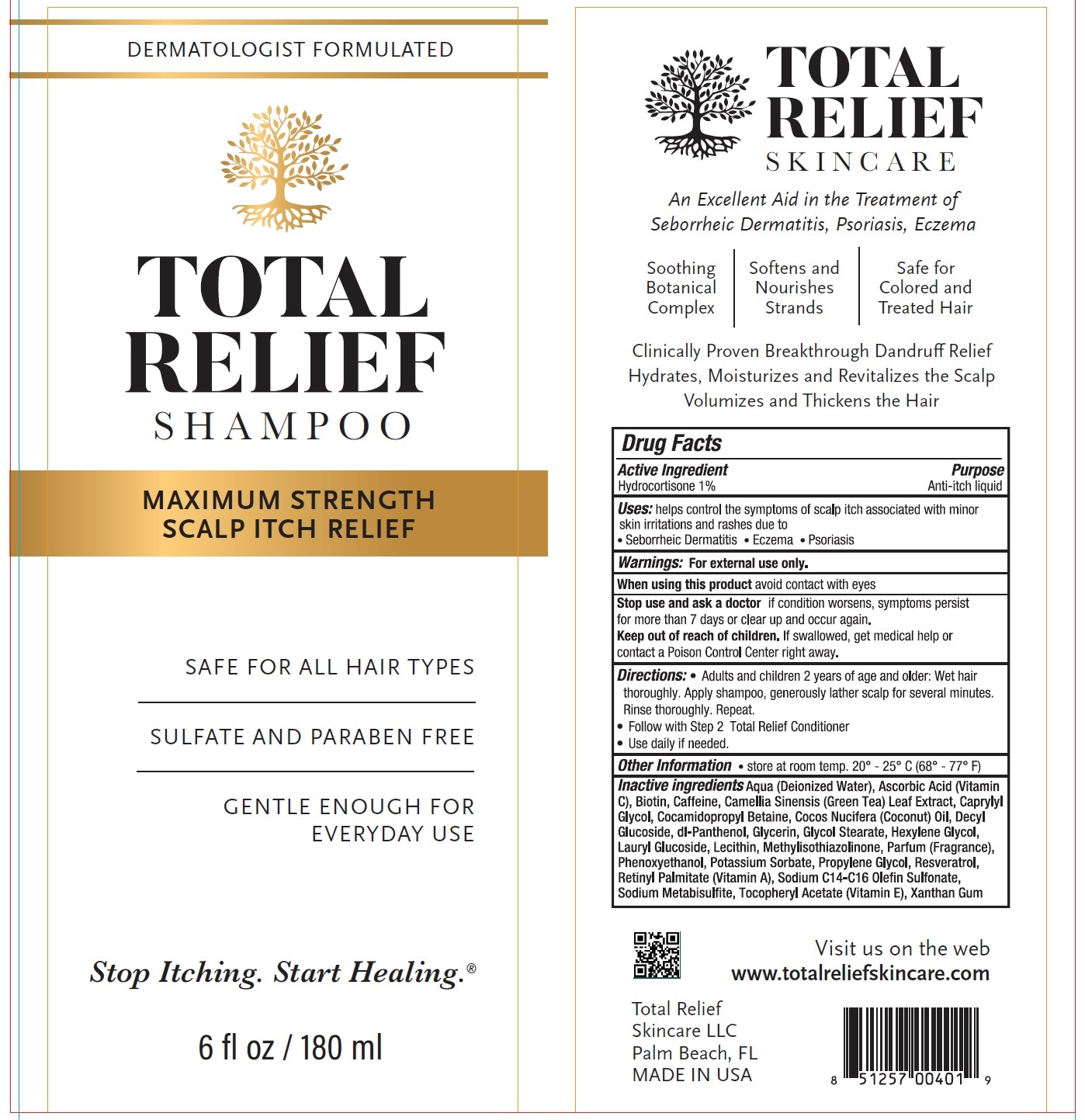 DRUG LABEL: TOTAL RELIEF
NDC: 71516-342 | Form: SHAMPOO
Manufacturer: DR. MARDER SKINCARE, LLC
Category: otc | Type: HUMAN OTC DRUG LABEL
Date: 20231111

ACTIVE INGREDIENTS: HYDROCORTISONE 10 mg/1 mL
INACTIVE INGREDIENTS: WATER; ASCORBIC ACID; BIOTIN; CAFFEINE; GREEN TEA LEAF; CAPRYLYL GLYCOL; COCAMIDOPROPYL BETAINE; COCONUT OIL; DECYL GLUCOSIDE; PANTHENOL; GLYCERIN; GLYCOL STEARATE; HEXYLENE GLYCOL; LAURYL GLUCOSIDE; METHYLISOTHIAZOLINONE; PHENOXYETHANOL; POTASSIUM SORBATE; PROPYLENE GLYCOL; RESVERATROL; VITAMIN A PALMITATE; SODIUM C14-16 OLEFIN SULFONATE; SODIUM METABISULFITE; .ALPHA.-TOCOPHEROL ACETATE; XANTHAN GUM

TOTAL RELIEF SHAMPOO

Active Ingredient

Hydrocortisone 1%

Purpose

Anti-itch liquid

Uses:

helps control the symptoms of scalp itch associated with minor skin irritations and rashes due to

- Seborrheic Dermatitis
- Eczema
- Psoriasis

Warnings:

For external use only.

When using this product

avoid contact with eyes

Stop use and ask a doctor

if condition worsens, symptoms persist for more than 7 days or clear up and occur again.

Keep out of reach of children.

If swallowed, get medical help or contact a Poison Control Center right away.

Directions:

- Adults and children 2 years of age and older: Wet hair thoroughly. Apply shampoo, generously lather scalp for several minutes. Rinse thoroughly, Repeat.
- Follow with Step 2 Total Relief Conditioner
- Use daily if needed.

Other Information

- store at room temp. 20° - 25° C (68° - 77° F)

Inactive ingredients

Aqua (Deionized Water), Ascorbic Acid (Vitamin C), Biotin, Caffeine, Camellia Sinensis (Green Tea) Leaf Extract, Caprylyl Glycol, Cocamidopropyl Betaine, Cocos Nucifera (Coconut) Oil, Decyl Glucoside, dl-Panthenol, Glycerin, Glycol Stearate, Hexylene Glycol, Lauryl Glucoside, Lecithin, Methylisothiazolinone, Parfum (Fragrance), Phenoxyethanol, Potassium Sorbate, Propylene Glycol, Resveratrol, Retinyl Palmitate (Vitamin A), Sodium C14-C16 Olefin Sulfonate, Sodium Metabisulfite, Tocopheryl Acetate (Vitamin E), Xanthan Gum